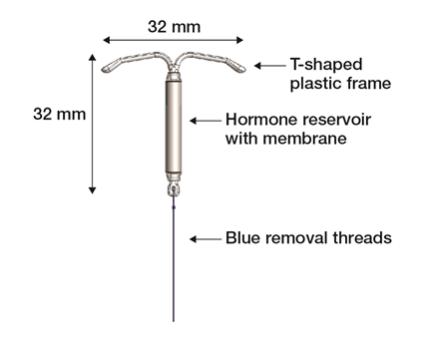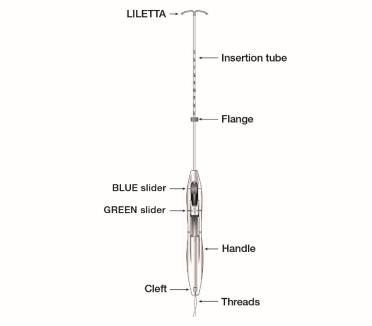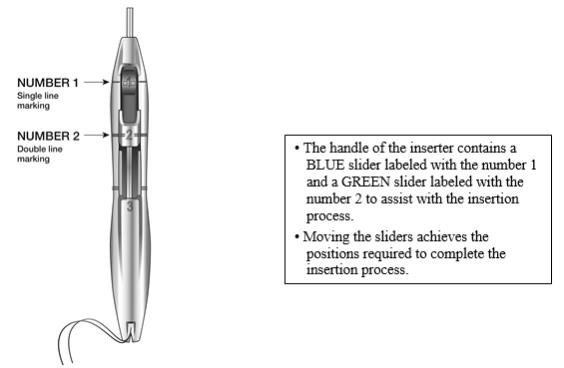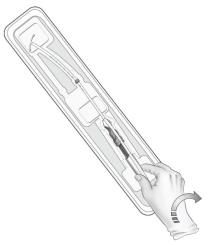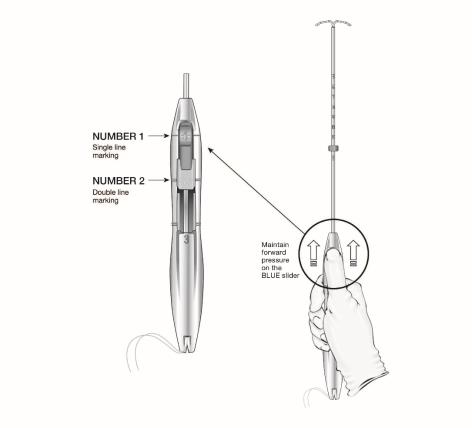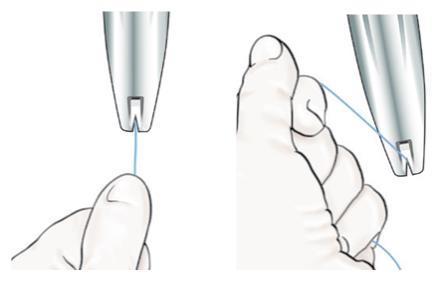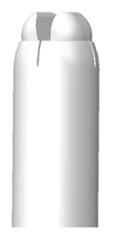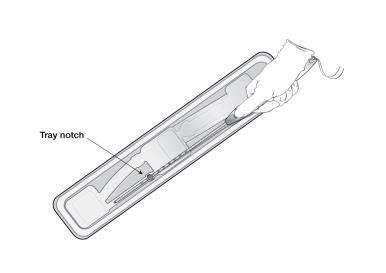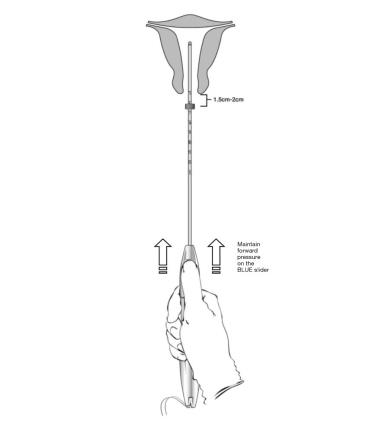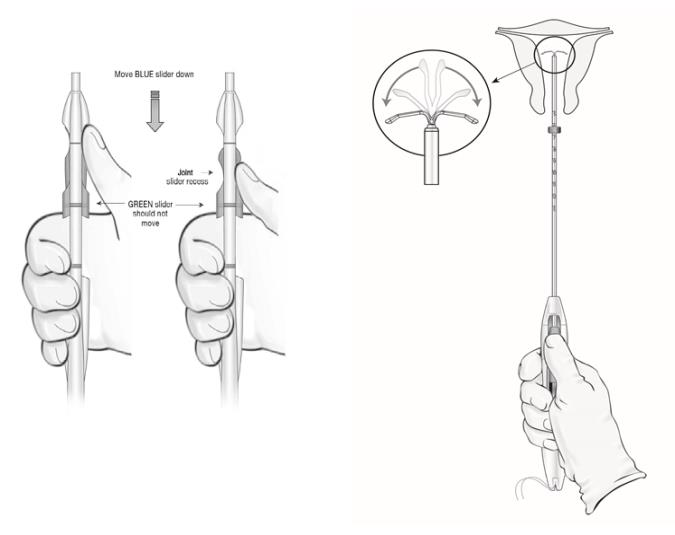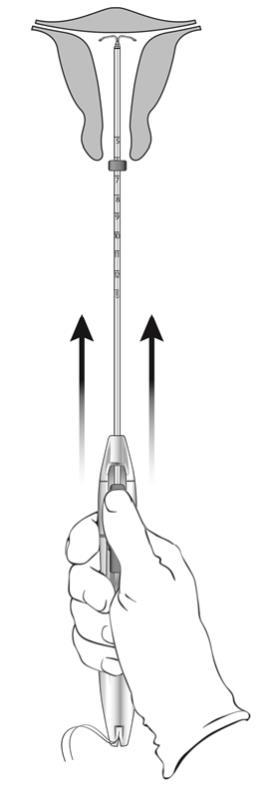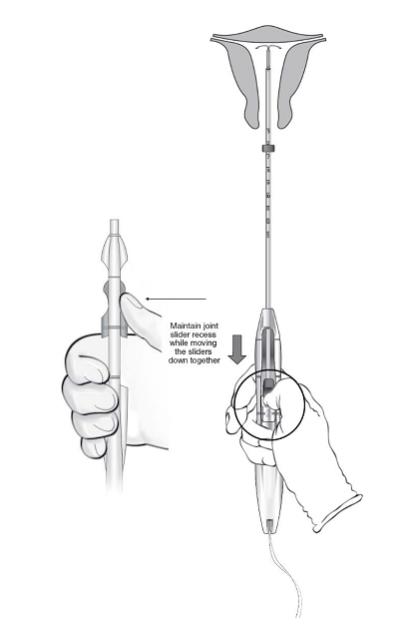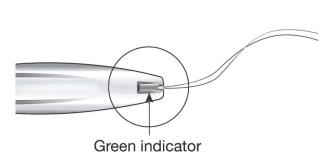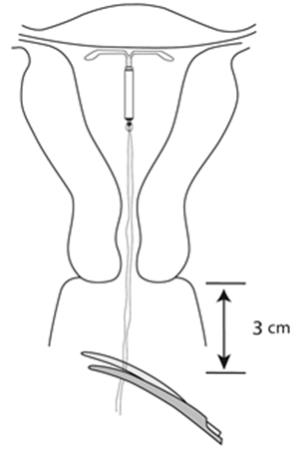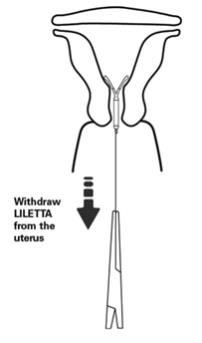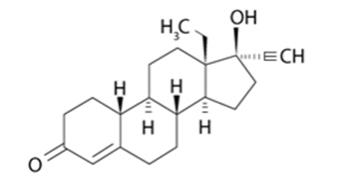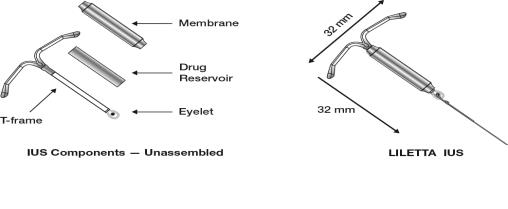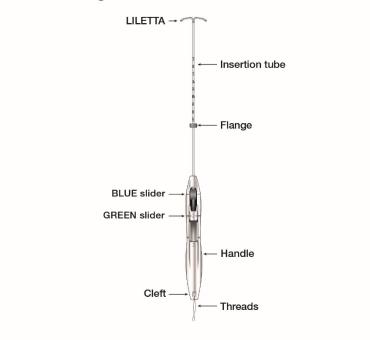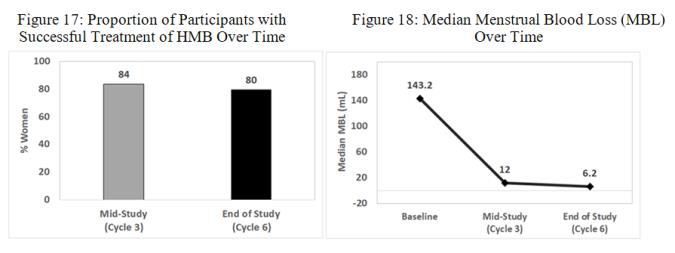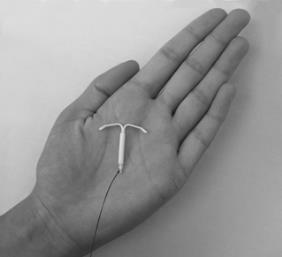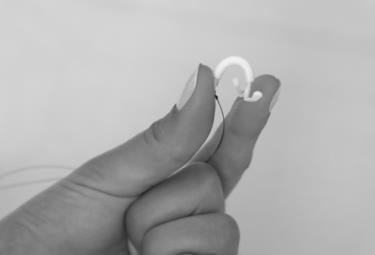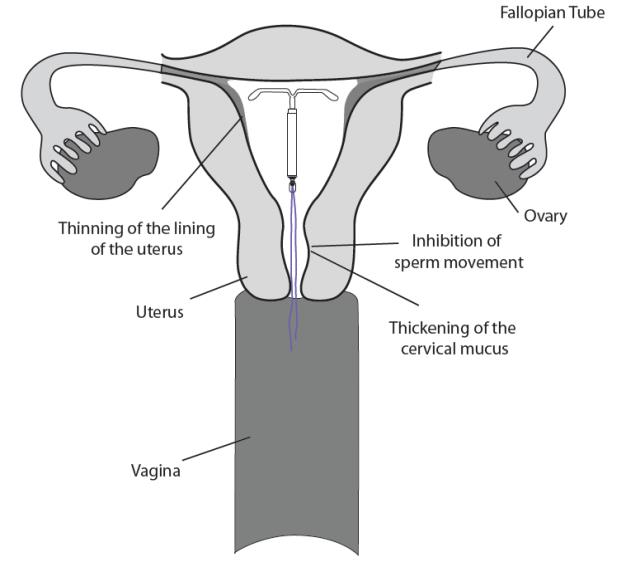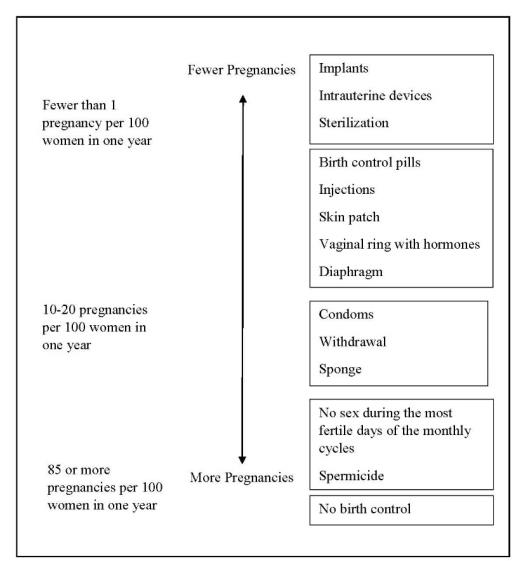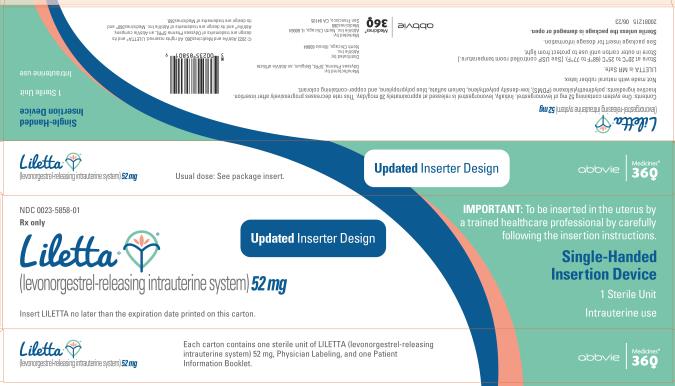 DRUG LABEL: LILETTA
NDC: 0023-5858 | Form: INTRAUTERINE DEVICE
Manufacturer: Allergan, Inc.
Category: prescription | Type: HUMAN PRESCRIPTION DRUG LABEL
Date: 20230629

ACTIVE INGREDIENTS: LEVONORGESTREL 52 mg/1 1
INACTIVE INGREDIENTS: DIMETHICONE; BARIUM SULFATE

HIGHLIGHTS OF PRESCRIBING INFORMATION

These highlights do not include all the information needed to use LILETTA® safely and effectively. See full prescribing information for LILETTA.
LILETTA (levonorgestrel-releasing intrauterine system)
Initial U.S. Approval: 1968 (norgestrel)

RECENT MAJOR CHANGES

Indications and Usage, Heavy Menstrual Bleeding (1.2) | 06/2023
Dosage and Administration, Dosing Over Time (2.1) | 06/2023
Dosage and Administration, Insertion Instructions (2.3) | 11/2022
Dosage and Administration, Removal of LILETTA (2.6) | 06/2023
Contraindications (4) | 06/2023
Warnings and Precautions, Expulsion (5.6) | 06/2023

1 INDICATIONS AND USAGE

LILETTA is a progestin-containing intrauterine system indicated for:

- Prevention of pregnancy for up to 8 years (1.1)
- Treatment of heavy menstrual bleeding for up to 5 years in patients who choose intrauterine contraception as their method of contraception (1.2)

2 DOSAGE AND ADMINISTRATION

- The initial release rate of levonorgestrel (LNG) is approximately 20 mcg/day and declines progressively to approximately 6.5 mcg/day after 8 years; LILETTA can be removed at any time but must be removed by the end of the eighth year. (2.1)
- To be inserted into the uterine cavity with the provided inserter by a trained healthcare professional using strict aseptic technique. Follow insertion instructions exactly as described. (2.3)
- Re-examination and evaluation should be considered 4 to 6 weeks after insertion and during routine care, or more often if clinically indicated. (2.5)

3 DOSAGE FORMS AND STRENGTHS

One intrauterine system consisting of a T-shaped polyethylene frame with a drug reservoir containing 52 mg LNG, packaged within a sterile inserter. (3)

4 CONTRAINDICATIONS

- Pregnancy (4)
- Use for post-coital contraception (emergency contraception) (4)
- Congenital or acquired uterine anomaly that distorts the uterine cavity and would be incompatible with correct IUS placement (4)
- Acute pelvic inflammatory disease (PID) (4)
- Postpartum endometritis or infected abortion in the past 3 months (4)
- Known or suspected uterine or cervical malignancy (4)
- Known or suspected breast cancer or other hormone-sensitive cancer (4)
- Uterine bleeding of unknown etiology (4)
- Untreated acute cervicitis or vaginitis or other lower genital tract infections (4)
- Acute liver disease or liver tumor (benign or malignant) (4)
- Increased susceptibility to pelvic infections (4)
- A previously inserted IUS that has not been removed (4)
- Hypersensitivity to any component of LILETTA (4)

5 WARNINGS AND PRECAUTIONS

- Remove LILETTA if pregnancy occurs with LILETTA in place and LILETTA is in the uterus. If pregnancy occurs, there is increased risk of ectopic pregnancy (including loss of fertility), pregnancy loss, septic abortion (including septicemia, shock, and death), and premature labor and delivery. (5.1, 5.2)
- Severe infection or sepsis, including Group A streptococcal sepsis (GAS), have been reported following insertion of LNG-releasing IUSs; strict aseptic technique is essential during insertion. (5.3)
- Before using LILETTA, consider the risks of pelvic infection. (5.4)
- Perforation may occur and reduce contraceptive effectiveness or require surgery. Risk is increased if inserted in patients who have fixed retroverted uteri, are postpartum, or are lactating. (5.5)
- Partial or complete expulsion may occur. (5.6)
- Evaluate persistent enlarged ovarian follicles or ovarian cysts. (5.7)
- Bleeding patterns can become altered, may remain irregular, and amenorrhea may ensue. (5.8)

6 ADVERSE REACTIONS

The most common adverse reactions reported in clinical studies (> 10% participants) are vulvovaginal mycotic infections, vaginal bacterial infections, acne, and nausea or vomiting. (6.1)

To report SUSPECTED ADVERSE REACTIONS, contact AbbVie at 1-800-678-1605 or FDA at 1-800-FDA-1088 or www.fda.gov/medwatch.

FULL PRESCRIBING INFORMATION

1 INDICATIONS AND USAGE

1.1 Contraception

LILETTA is indicated for prevention of pregnancy for up to 8 years.

1.2 Heavy Menstrual Bleeding

LILETTA is indicated for the treatment of heavy menstrual bleeding for up to 5 years in patients who choose to use intrauterine contraception as their method of contraception; replace after the end of the fifth year if continued treatment of heavy menstrual bleeding is needed.

2 DOSAGE AND ADMINISTRATION

2.1 Dosing Over Time

LILETTA contains 52 mg of levonorgestrel (LNG). Initially, LNG is released in vivo at a rate of approximately 20 mcg/day. This rate decreases progressively to approximately 6.5 mcg/day after 8 years. The average in vivo release rate of LNG is approximately 13.5 mcg/day over a period of 8 years.

For contraception, remove LILETTA by the end of the eighth year. LILETTA can be replaced at the time of removal with a new LILETTA if continued contraceptive protection is desired.

For treatment of heavy menstrual bleeding, replace LILETTA by the end of the fifth year if continued use is needed.

2.2 Timing of Insertion

Refer to Table 1 for instructions on when to start use of LILETTA.

Table 1: When to Insert LILETTA
Starting LILETTA in patients not currently using hormonal or intrauterine contraception | - LILETTA can be inserted any time there is reasonable certainty the patient is not pregnant. Consider the possibility of ovulation and conception prior to initiation of LILETTA [see Contraindications (4)]. - If LILETTA is inserted after the first 7 days of the menstrual cycle, the patient should use a barrier method of contraception (such as condoms) or abstain from vaginal intercourse for 7 days after insertion to prevent pregnancy.
Switching to LILETTA from an oral, transdermal, or vaginal hormonal contraceptive | - LILETTA may be inserted at any time during the hormone-free interval of the previous method. - If LILETTA is inserted during active use of the previous method, continue that method for 7 days after LILETTA insertion or until the end of the current treatment cycle. - If using continuous hormonal contraception, discontinue that method 7 days after LILETTA insertion.
Switching to LILETTA from an injectable progestin contraceptive | - LILETTA may be inserted at any time. - If LILETTA is inserted more than 3 months (13 weeks) after the last injection, the patient should use a barrier method of contraception (such as condoms) or abstain from vaginal intercourse for 7 days after insertion to prevent pregnancy.
Switching to LILETTA from a contraceptive implant or another IUS | - Insert LILETTA on the same day the implant or IUS is removed. - This switch to LILETTA may be at any time during the menstrual cycle. Back-up contraception is not needed.
Inserting LILETTA after pregnancy
- After first-trimester abortion or miscarriage | - LILETTA may be inserted immediately after a first-trimester surgical or completed medical abortion or miscarriage, unless it is a septic abortion [see Contraindications (4)]. Back-up contraception is not needed.
- After childbirth or second-trimester abortion or miscarriage | - If immediate, insert LILETTA after expulsion/removal of the placenta, unless infection is present. [See Contraindication (4), Warnings and Precautions (5.5, 5.6), Adverse Reactions (6.1)] Back-up contraception is not needed. - If not immediate: - Delay inserting LILETTA a minimum of 4 weeks or until the uterus is fully involuted [see Warnings and Precautions (5.5, 5.6), Adverse Reactions (6.1)]. - If the patient has not yet had a period, consider the possibility of ovulation and conception occurring prior to insertion of LILETTA [see Contraindications (4), Warnings and Precautions (5.2), and FDA-Approved Patient Labeling]. LILETTA can be inserted any time there is reasonable certainty the patient is not pregnant. - If LILETTA is not inserted during the first 7 days of the menstrual cycle, the patient should use a barrier method of contraception (such as condoms) or abstain from vaginal intercourse for 7 days after insertion to prevent pregnancy [see Contraindications (4), Warnings and Precautions (5.2)].; The risk of perforation may be increased if an IUS is inserted in a lactating woman [see Warnings and Precautions (5.5)].

2.3 Insertion Instructions

LILETTA (Figure 1a) is provided in a tray, sealed with a peel-off lid and is inserted into the uterine cavity with the provided inserter (Figure 1b) [see Description (11)] by carefully following the insertion instructions. Do not use if the seal of the sterile package is broken or appears compromised. Use strict aseptic techniques throughout the insertion procedure [see Warnings and Precautions (5.3)]. LILETTA is for single use only.

Note: The inserter provided with LILETTA (see Figure 1b) and the Insertion Instructions in this section are not applicable for immediate insertion after childbirth or second-trimester abortion or miscarriage. For immediate insertion, remove LILETTA from the inserter by pulling LILETTA out of the top of the inserter and insert according to accepted practice.

Figure 1 a: LILETTA Intrauterine Contraceptive System (IUS)

Figure 1b: LILETTA IUS with Inserter

The LILETTA IUS is packaged partially preloaded within the inserter. The threads are passed through the insertion tube and exit through an opening in the handle at the cleft.

The handle of the inserter contains a BLUE slider labeled with the number 1 and a GREEN slider labeled with the number 2. The handle is labeled with the number 3. The sliders are labeled with the numbers 1 and 2, and the handle is labeled with the number 3 to assist with the insertion process (Figure 2). Moving the sliders achieves the positions required to complete the insertion process.

Figure 2: Inserter Sliders

Planning for Insertion

LILETTA should only be inserted by a trained healthcare professional. Healthcare professionals should become thoroughly familiar with the product, product educational materials, product insertion instructions, prescribing information, and patient labeling before attempting insertion of LILETTA.

Obtain a complete medical and social history to determine conditions that might influence the selection of LILETTA for contraception. If indicated, perform a physical examination and appropriate tests for genital or sexually transmitted infections.^1 [See Contraindications (4) and Warnings and Precautions (5.4, 5.10)].

Check the expiration date on the box before opening it. Do not insert LILETTA after the expiration date.

Visually inspect the packaging containing LILETTA to verify that the packaging has not been damaged (e.g., torn, punctured, etc.). If the packaging has any visual damage that could compromise sterility, do not use the unit for insertion [see Warnings and Precautions (5.3)]. Complete the pelvic examination, speculum placement, tenaculum placement, and sounding of the uterus before opening the LILETTA packaging.

Do not open the packaging to insert LILETTA if the following clinical findings occur:

- the cervix is unable to be properly visualized
- the uterus cannot be adequately instrumented (during sounding)
- the uterus sounds to less than 5.5 cm

Preparation for Insertion

Ensure all needed items for LILETTA insertion are readily available:

- Gloves
- Sterile speculum
- Sterile uterine sound
- Sterile tenaculum
- Antiseptic solution
- LILETTA with inserter tray, sealed with a peel-off lid
- Sterile, blunt-tipped scissors

Additional items may be useful:

- Local anesthesia, needle, and syringe
- Sterile os finder and/or cervical dilators
- Ultrasound with abdominal probe

Exclude pregnancy and confirm that there are no other contraindications to the insertion and use of LILETTA.

Follow the insertion instructions exactly as described to ensure proper insertion.

If you encounter cervical stenosis at any time during uterine sounding or LILETTA insertion, use cervical dilators, not force, to overcome resistance. If necessary, dilation, sounding, and insertion may be performed with ultrasound guidance.

Insertion may be associated with some pain and/or bleeding or vasovagal reactions (e.g., diaphoresis, syncope, bradycardia, or seizure), especially in patients with a predisposition to these conditions. Consider administering analgesics prior to insertion.

Use aseptic technique during the entire insertion procedure.

Insertion Procedure

The overall insertion process is conducted in 5 steps.

Step 1 – Preparation of Patient for Insertion

- With the patient comfortably in lithotomy position, do a bimanual exam to establish the size, shape, and position of the uterus and to evaluate any signs of uterine infection.
- Gently insert a speculum to visualize the cervix.
- Thoroughly cleanse the cervix and vagina with antiseptic solution.
- Administer cervical anesthetic, if needed.
- Apply a tenaculum to the cervix and use gentle traction to align the cervical canal with the uterine cavity. If the uterus is retroverted, it may be more appropriate to grasp the lower lip of the cervix. Keep the tenaculum in position and maintain gentle traction on the cervix throughout the insertion procedure.
- Carefully sound the uterus to measure its depth.
- The uterus should sound to a depth of at least 5.5 cm. Insertion of LILETTA into a uterine cavity that sounds to less than 5.5 cm may increase the incidence of expulsion, bleeding, pain, perforation, and possibly pregnancy. LILETTA should not be inserted if the uterus sounds to less than 5.5 cm.
- After ascertaining that the patient is appropriate for LILETTA, replace contaminated glove(s) and open the packaging containing LILETTA, noting the lot number.

Step 2 – Opening the Sterile LILETTA Packaging

- Remove the sealed tray containing LILETTA from the box.
- Inspect the sealed tray and do not use the product if the packaging, inserter, or IUS is damaged.
- Lay the tray on a flat surface with the peel-off lid side up.
- Remove peel-off lid.

Step 3 – Loading LILETTA into the Inserter

- To remove the inserter from the tray, grasp the handle below the sliders and twist gently (Figure 3).
  - NOTE: Do not attempt to remove the inserter by pulling on the tube.

Figure 3: Removing Inserter from Tray

- Ensure both sliders (labeled 1 and 2) are fully forward (Figure 4):
  - The BLUE slider (labeled with the number 1) has a single line marking that will align with the handle’s single line marking.
  - The GREEN slider (labeled with the number 2) has a double line marking that will align with the handle’s double line marking.

- Grip the handle keeping your thumb or finger in the groove of the BLUE slider (over the numeral 1) and apply forward pressure while ensuring both sliders are fully forward.

Figure 4: Sliders Completely Forward for Loading LILETTA

- Load LILETTA into the inserter:
  - Ensure the arms of the IUS are horizontal (aligned to the horizontal plane of the handle and flange); adjust the rotation of the IUS as needed using the flat sterile surface of the tray.
  - While maintaining forward pressure on the BLUE slider, gently pull the threads straight back to load LILETTA into the insertion tube. Ensure even tension is applied to both threads when pulling.
  - Pull the threads upward or downward to lock the threads into the cleft at the bottom end of the handle (Figure 5); you must lock the threads in the cleft to prevent the IUS from moving out of the top of the insertion tube. Once the threads are locked in the cleft, stop holding the threads.
  - After the IUS is loaded, continue to sustain forward pressure on the BLUE slider to maintain a hemispherical dome with the tips of the IUS.

- When correctly loaded, the IUS is completely within the insertion tube with the tips of the arms forming a hemispherical dome at the top of the tube (Figure 6).
- If the IUS is not correctly loaded, do not attempt insertion.
- To re-load LILETTA:
  ▪ Pull the BLUE slider back with your thumb until the groove becomes aligned with the GREEN slider to release the IUS.
  ▪ Manually pull the threads out of the cleft.
  ▪ Return the BLUE slider to the forward position and repeat the loading steps.

Figure 5: Locking the Threads in Cleft

Figure 6: Close-up of Hemispherical Dome at Tip of Tube

- Adjust the flange to the measured uterine depth based on sounding. To adjust, place the flat side of the flange in the tray notch (Figure 7) or against a sterile edge inside of the tray. Slide the insertion tube as necessary to move the flange to the correct measurement. Ensure the flat sides of the flange are in the same horizontal plane as the handle. If, at any step, there is a need to touch the flange or another sterile surface, sterile gloves should be used.

Figure 7: Adjusting the Flange

- If an adjustment to the curvature of the insertion tube is required to accommodate the anatomical orientation of the uterus, you may bend or straighten the insertion tube, but do not touch above the flange unless using sterile gloves. When bending the tube, avoid sharp bends to prevent kinking.
- Once the flange has been properly positioned, avoid contact of flange against objects that can change its position (e.g., tray, speculum, tenaculum, etc.).

Step 4 – Inserting LILETTA into the Uterus

- Apply gentle traction on the tenaculum and continue to apply forward pressure on the BLUE slider while inserting the loaded insertion tube through the cervical os. Advance the tube until the upper edge of the flange is 1.5-2 cm from the external cervical os (Figure 8). Maintain forward pressure on the BLUE slider throughout the insertion process.
  ○ DO NOT advance flange to the cervix at this time.
  ○ DO NOT force the inserter. If necessary, dilate the cervical canal.

Figure 8: Advancing Insertion Tube until Flange is 1.5 to 2 cm from the External Cervix

● Using your thumb or finger, gently slide only the BLUE slider back. You will feel slight resistance initially to move the BLUE slider out of its starting position. Continue to move the BLUE slider back until you feel slight resistance again as the BLUE and GREEN sliders will merge together to form a joint slider recess. Do not move the BLUE slider any more than is necessary to create the recess. Maintain the GREEN slider so that the double line markings on the slider and the insertion handle remain aligned (Figure 9). This will allow the IUS arms to open in the lower uterine segment. Do not pull the sliders back any further as this could result in premature release of the IUS at the incorrect location.

Figure 9: Releasing and Opening the Arms of the IUS

- Wait 10-15 seconds to allow for the arms of the IUS to fully open.
- Without moving the sliders, advance the inserter until the flange touches the cervix. If fundal resistance is encountered, do not continue to advance. LILETTA is now in the fundal position (Figure 10).
- Note: Fundal position is important to prevent expulsions.

Figure 10: Move LILETTA into the Fundal Position

Step 5 – Releasing LILETTA and Procedure Completion

- While holding the inserter steady and maintaining its position relative to the cervix, move both sliders (BLUE and GREEN) together while maintaining the joint slider recess down toward the number 3 on the handle (Figure 11) until a click is heard and the GREEN indicator at the bottom of the handle is visible, signifying deployment (Figure 12).

Figure 11: Releasing LILETTA from the Inserter Tube

- Look at the cleft to ensure the threads were properly released (Figure 12); if not released or if a click is not heard, grasp the threads and gently pull the threads out of the cleft.

Figure 12: Green Indicator Visible and Threads Released from Cleft

- Withdraw the inserter from the uterus.
- Use blunt-tipped sharp scissors to cut the IUS threads perpendicular to the thread length, leaving about 3 cm outside of the cervix (Figure 13). Note: Do not cut threads at an angle as this may leave sharp ends.
- Do not apply tension or pull on the threads when cutting to prevent displacing the IUS.

Figure 13: Cut the Threads about 3 cm from the Cervix

- Insertion of LILETTA is now complete.

Important information to consider during or after insertion:

If you suspect the IUS is not in the correct position, conduct the following procedures:

- Check insertion with an ultrasound or other appropriate radiologic test.
- If incorrect insertion is confirmed, remove LILETTA. Do not reinsert the same LILETTA IUS after removal.

Difficult Insertion

If insertion is difficult because the uterus cannot be appropriately instrumented, consider the following measures:

- Use of cervical anesthesia to make sounding and manipulation more tolerable.
- Use of dilators to dilate the cervix if needed to allow passage of the sound or inserter.
- Abdominal ultrasound guidance during dilation and/or insertion.
- If there is clinical concern, exceptional pain, or bleeding during or after insertion, take appropriate steps, such as physical examination and ultrasound, immediately to exclude uterine perforation [see Warnings and Precautions (5.5)].

2.4 Patient Counseling and Record-Keeping

Counsel the patient on what to expect following LILETTA insertion. Discuss expected bleeding patterns with LILETTA use. Review the signs and symptoms associated with infection, perforation, and expulsion that may occur with use of LILETTA [see Patient Counseling Information (17)].

Prescribe analgesics, if indicated.

2.5 Patient Follow-Up

The healthcare professional should consider re-examining and evaluating patients 4 to 6 weeks after insertion and during routine care, or more frequently if clinically indicated. The IUS threads should be checked during each evaluation.

2.6 Removal of LILETTA

Planning and Timing of Removal

If pregnancy is desired, LILETTA can be removed at any time.

If pregnancy is not desired, LILETTA can be removed at any time; however, a contraception method should be started prior to removal of LILETTA [see Dosage and Administration (2.5)]. Counsel patients that they are at risk of pregnancy if they had intercourse in the week prior to removal without use of a backup contraceptive method.

For contraception, LILETTA should be removed after 8 years. LILETTA can be replaced at the time of removal with a new LILETTA if continued contraceptive protection is desired.

For treatment of heavy menstrual bleeding, LILETTA should be replaced at the end of the fifth year if continued treatment is needed.

Preparation for Removal

Ensure all needed items for LILETTA removal are readily available:

- Gloves
- Sterile speculum
- Sterile forceps

Additional items may be required:

- Local anesthetic, needle, and syringe
- Sterile os finder and/or cervical dilators
- Ultrasound with abdominal transducer
- Sterile tenaculum
- Antiseptic solution
- Sterile long, narrow forceps or intrauterine thread retriever

Removal may be associated with some pain and/or bleeding or vasovagal reactions (e.g., syncope, bradycardia, or seizure), especially in patients with a predisposition to these conditions.

After removal of LILETTA, examine the system to ensure that it is intact. The hormone cylinder may slide over and cover the horizontal arms, giving the appearance of missing arms. This does not require further intervention if the system is verified to be intact.

Breakage, embedment in the myometrium, or perforation of LILETTA can make removal difficult [see Warnings and Precautions (5.5)]. IUS breakage may be associated with removal. Analgesia, paracervical anesthesia, cervical dilation, alligator forceps or other grasping instrument, or hysteroscopy may assist in removal.

Removal Procedure

With the patient comfortably in lithotomy position, place a speculum and visualize the cervix.

When the threads of LILETTA are visible:

- Remove the IUS by applying gentle traction on the threads with forceps (Figure 14).
- The arms of the device will fold upward as it is withdrawn from the uterus.
- If the IUS cannot be removed with gentle traction on the threads, perform an ultrasound examination to confirm location of the IUS, including assessment for embedment in the myometrium or partial- or total-perforation. If the IUS is in the uterus, use long, narrow forceps to grasp LILETTA. Consider use of a tenaculum, cervical anesthesia, cervical dilators, and/or ultrasound guidance as needed.
- After removal, examine the system to ensure it is intact.

If the threads of LILETTA are not visible:

- Determine location of the IUS and exclude embedment or perforation by ultrasound examination [see Warnings and Precautions (5.10)].
- If the IUS is in the uterine cavity, thoroughly cleanse the cervix and vagina with antiseptic solution. Use a thread retriever to capture the threads or a long, narrow forceps (e.g., Alligator forceps) to grasp LILETTA. Consider use of a tenaculum, cervical anesthesia, cervical dilators, and/or ultrasound guidance as needed. If LILETTA cannot be removed using the above techniques, consider hysteroscopic evaluation for removal.
- If the IUS is not in the uterine cavity, consider an abdominal x-ray or CT scan to evaluate if the IUS is in the abdominal cavity. Consider laparoscopic evaluation for removal, as clinically indicated.
- After removal, examine the system to ensure it is intact.

Figure 14: Removal of LILETTA

2.7 Continuation of Contraception after Removal

If a patient wishes to continue using LILETTA or another intrauterine contraceptive, insertion can occur immediately after removal.

If a patient with regular cycles wants to start a different birth control method, time the removal and initiation of a new method to ensure continuous contraception. Either remove LILETTA during the first 7 days of the menstrual cycle and start the new method or start the new method at least 7 days prior to removing LILETTA if removal is to occur at other times during the cycle.

If a patient with irregular cycles or amenorrhea wants to start a different birth control method, start the new method at least 7 days before LILETTA removal.

If LILETTA is removed but no other contraceptive method has already been started, the new contraceptive method can be started on the day LILETTA is removed. The patient should use a backup barrier method of contraception (e.g., condoms) or abstain from vaginal intercourse for 7 days to prevent pregnancy.

3 DOSAGE FORMS AND STRENGTHS

LILETTA is a levonorgestrel-releasing intrauterine system consisting of a T-shaped polyethylene frame with a drug reservoir containing 52 mg levonorgestrel, packaged within a sterile inserter.

4 CONTRAINDICATIONS

LILETTA is contraindicated when one or more of the following conditions exist:

Pregnancy [see Use in Specific Populations (8.1)]

For use as post-coital contraception (emergency contraception)

Congenital or acquired uterine anomaly, including leiomyomas, that distorts the uterine cavity and would be incompatible with correct IUS placement [see Warnings and Precautions (5.10)]

Acute pelvic inflammatory disease (PID) [see Warnings and Precautions (5.4)]

Postpartum endometritis or infected abortion in the past 3 months [see Warnings and Precautions (5.2, 5.4)]

Known or suspected uterine or cervical malignancy

Known or suspected breast cancer or other hormone-sensitive cancer, now or in the past [see Warnings and Precautions (5.9)]

Uterine bleeding of unknown etiology [see Warnings and Precautions (5.10)]

Untreated acute cervicitis or vaginitis, including bacterial vaginosis, known chlamydial or gonococcal cervical infection, or other lower genital tract infections until infection is controlled [see Warnings and Precautions (5.4)]

Acute liver disease or liver tumor (benign or malignant)

Conditions associated with increased susceptibility to pelvic infections [see Warnings and Precautions (5.4)]

A previously inserted IUS that has not been removed

A history of hypersensitivity reaction to any component of LILETTA. Reactions may include rash, urticaria, and angioedema [see Adverse Reactions (6.2)].

5 WARNINGS AND PRECAUTIONS

5.1 Ectopic Pregnancy

Evaluate patients for ectopic pregnancy if they become pregnant with LILETTA in place because the likelihood of a pregnancy being ectopic is increased with use of an IUS. Approximately half of pregnancies that occur with an IUS in place are likely to be ectopic. Also consider the possibility of ectopic pregnancy in the case of lower abdominal pain, especially in association with missed menses or new onset bleeding in an amenorrheic patient. If an ectopic pregnancy is confirmed, LILETTA should be removed.

The incidence of ectopic pregnancy in the clinical study on contraception with LILETTA, which excluded participants with a history of ectopic pregnancy who did not have a subsequent intrauterine pregnancy, was approximately 0.12 per 100 women-years. There were no ectopic pregnancies in the clinical study on heavy menstrual bleeding with LILETTA. The risk of ectopic pregnancy in patients who have a history of ectopic pregnancy and use LILETTA is unknown. Patients with a previous history of ectopic pregnancy, tubal surgery, or pelvic infection have a higher risk of ectopic pregnancy. Ectopic pregnancy may require surgery and may result in loss of fertility.

Patients who use LILETTA should be informed about recognizing the signs and symptoms of ectopic pregnancy and promptly reporting them to their healthcare professional, and about the associated risks of ectopic pregnancy (e.g., loss of fertility).

5.2 Intrauterine Pregnancy

If pregnancy occurs while using LILETTA, determine if LILETTA is in the uterus. If LILETTA is in the uterus, attempt to remove LILETTA because leaving it in place may increase the risk of spontaneous abortion and preterm labor. Removal of LILETTA or probing of the uterus may also result in spontaneous abortion. In the event of an intrauterine pregnancy with LILETTA, consider the following:

Septic Abortion

If a patient becomes pregnant with an IUS in place, septic abortion—potentially including septicemia, septic shock, and death—may occur. Septic abortion typically requires hospitalization and treatment with intravenous antibiotics. Septic abortion may result in spontaneous abortion or a medical indication for pregnancy termination. Should severe infection of the uterus occur, hysterectomy may be required, which will result in permanent infertility. LILETTA is contraindicated in patients who have had an infected abortion in the prior 3 months.

Continuation of Pregnancy

If a patient becomes pregnant with LILETTA in place and if LILETTA cannot be removed or the patient chooses not to have it removed, warn the patient that failure to remove LILETTA increases the risk of miscarriage, sepsis, premature labor, and premature delivery. Prenatal care should include counseling about these risks and instructions to immediately report any flu-like symptoms, fever, chills, cramping, pain, bleeding, vaginal discharge or leakage of fluid, or any other symptom that suggests complications of the pregnancy.

5.3 Sepsis

Severe infection or sepsis, including Group A streptococcal sepsis (GAS), have been reported following insertion of LNG-releasing IUSs. In some cases, severe pain occurred within hours of insertion followed by sepsis within days. Because death from GAS is more likely if treatment is delayed, it is important to be aware of these rare but serious infections. Aseptic technique during insertion of LILETTA is essential to minimize serious infections such as GAS.

5.4 Pelvic Inflammatory Disease or Endometritis

Insertion of LILETTA is contraindicated in the presence of known or suspected PID or endometritis. As well, it is contraindicated in patients with untreated acute cervicitis or vaginitis (including bacterial vaginosis), known chlamydial or gonococcal cervical infection, or other known lower genital tract infections, until the infection is controlled. IUSs have been associated with an increased risk of PID, most likely due to organisms being introduced into the uterus during insertion. Assess risk factors for infection accordingly.

Patients who use LILETTA should be counseled to promptly notify a healthcare professional if they develop lower abdominal or pelvic pain, fever, chills, unusual or malodorous discharge, unexplained bleeding, genital lesions or sores, or dyspareunia. In such circumstances, perform a pelvic examination promptly to evaluate for possible pelvic infection. Remove LILETTA in cases of recurrent PID or endometritis, or if an acute pelvic infection is severe or does not respond to treatment.

In the clinical study on contraception with LILETTA, pelvic infection was diagnosed in 0.8% of participants. Pelvic infection was diagnosed as PID in 0.5% of participants and as endometritis in 0.3% of participants. Infections occurred following variable duration-of-use. One participant diagnosed with PID and two participants diagnosed with endometritis developed the infection within a week of LILETTA insertion. One case of endometritis was diagnosed at 39 days after LILETTA insertion. The remaining 11 cases of PID and endometritis were diagnosed more than six months after insertion, including one at 30 days after IUS removal. In the clinical study on heavy menstrual bleeding with LILETTA, there was one participant diagnosed with PID approximately 5 months after LILETTA insertion.

Patients at Increased Risk for PID or Endometritis

PID and endometritis are often associated with a sexually transmitted infection (STI), and LILETTA does not protect against STIs. The risk of PID or endometritis is greater for patients who have multiple sexual partners, and for patients whose sexual partner(s) have multiple sexual partners. Patients who have had PID or endometritis are at increased risk for recurrence or re-infection. Other risk factors for these infections include unprotected sex and acquired immune deficiency syndrome (AIDS).

Asymptomatic PID or Endometritis

PID or endometritis may be asymptomatic but still result in tubal damage and its sequelae.

Treatment of PID or Endometritis

In IUS users with suspected or diagnosed PID or endometritis, obtain microbial specimens, including those for sexually transmitted infections, and initiate antibiotic treatment promptly. After initiation of antibiotic treatment, the IUS may be removed or kept in place. The patient should continue to receive antibiotic treatment according to current recommendations and should have close clinical follow-up. Guidelines for PID or endometritis treatment are available from the Centers for Disease Control (CDC), Atlanta, Georgia. ^1

If the patient opts for discontinuing IUS use, remove LILETTA after initiation of antibiotic treatment to avoid the potential risk for bacterial spread resulting from the removal procedure.

If the patient opts for ongoing IUS contraception, the patient may forego immediate removal of LILETTA after initiation of antibiotic treatment. However, the patient should have close clinical follow-up. If no clinical improvement occurs within 48–72 hours of initiating treatment, IUS removal is appropriate with continued antibiotic therapy, as indicated.

In the LILETTA clinical study on contraception, 12 of the 14 participants who developed PID or endometritis were successfully treated without removal of LILETTA (one of the 14 participants developed PID 30 days after removal).

Actinomycosis

Actinomycosis has been associated with IUS use. Symptomatic patients with known actinomycosis infection should have LILETTA removed and receive antibiotics. Actinomycetes can be found in the genital tract cultures in healthy patients without IUSs. The significance of actinomyces-like organisms on Pap test in an asymptomatic IUS user is unknown, and so this finding alone does not always require LILETTA removal and treatment. When possible, confirm a Pap test diagnosis with cultures.

5.5 Perforation

Perforation (total or partial, including penetration/embedment of LILETTA in the uterine wall or cervix) may occur, most often during insertion, although the perforation may not be detected until sometime later. Perforation may also occur at any time during IUS use. Perforation may reduce contraceptive efficacy and result in pregnancy. This may be associated with severe pain and continued bleeding.

The risk of perforation may be increased if an IUS is inserted when the uterus is fixed retroverted or not completely involuted during the post-partum period. Delay LILETTA insertion a minimum of four weeks or until involution is complete following a delivery or a second trimester abortion.

If perforation is suspected the IUS should be removed as soon as possible, surgery may be required. Delayed detection or removal of LILETTA in case of perforation may result in migration outside the uterine cavity, adhesions, peritonitis, intestinal perforations, intestinal obstruction, abscesses, and erosion of adjacent viscera.

In a large prospective comparative non-interventional cohort study with another IUS the incidence of uterine perforation was reported as 6.3 per 1,000 insertions for lactating participants, compared to 1.0 per 1,000 insertions for non-lactating participants.

The incidence of perforation during or following LILETTA insertion in the clinical studies, which excluded breastfeeding participants, was 0.1%.

5.6 Expulsion

Partial or complete expulsion of LILETTA may occur, resulting in the loss of contraceptive protection. In the clinical study on contraception with LILETTA, an overall expulsion rate of 4.1% over 8 years was reported, with a rate of 2.4% in nulliparous participants and 6.4% in parous participants. The majority (70.4%) occur in the first 12 months, with 23.9% occurring in the first three months and 42.3% in the first six months, cumulatively. Risk of expulsion is increased for patients with a history of heavy menstrual bleeding or greater than normal BMI at the time of insertion. In the clinical study on heavy menstrual bleeding with LILETTA, 8.6% of participants experienced expulsions, with two-thirds occurring within the first 90 days. About 90% of the expulsions occurred in overweight or obese participants.

Expulsion may be associated with symptoms of bleeding or pain, or it may be asymptomatic and go unnoticed. LILETTA typically decreases menstrual bleeding over time; therefore, an increase in menstrual bleeding may be indicative of an expulsion. Consider further diagnostic imaging, such as sonography or X-ray, to confirm expulsion if LILETTA is not found in the uterus.

The risk of expulsion is increased with insertions performed immediately after delivery; it appears to be increased with insertions performed after second-trimester abortion, based on limited data.

Remove a partially expelled LILETTA. If expulsion has occurred, a new LILETTA may be inserted when there is reasonable certainty the patient is not pregnant.

5.7 Ovarian Cysts

The contraceptive effect of LILETTA is mainly due to its local effects within the uterus; therefore, ovulatory cycles with follicular rupture usually occur in patients of fertile age using LILETTA. Most ovarian cysts that occur during use of LNG-releasing IUSs are asymptomatic and disappear spontaneously during two to three months of observation. Cysts that cause clinical symptoms can result in pelvic or abdominal pain or dyspareunia. In the clinical study on contraception, symptomatic ovarian cysts occurred in 4.7% of participants using LILETTA over the course of 8 years, and 0.3% of participants discontinued use of LILETTA because of an ovarian cyst. In the clinical study on heavy menstrual bleeding, symptomatic ovarian cysts occurred in 1.0% of participants using LILETTA over the course of 6 months.

Evaluate persistent ovarian cysts. Surgical intervention is not usually required, but may be necessary in some cases, and occurred in 1 (0.06%) of participants in the LILETTA study. Discuss this risk with patients, as indicated.

5.8 Bleeding Pattern Alterations

LILETTA can alter the bleeding pattern and result in spotting, irregular bleeding, heavy bleeding, oligomenorrhea, and amenorrhea. During the first three to six months of LILETTA use, the number of bleeding and spotting days may increase and irregular bleeding patterns may develop. Thereafter, the number of bleeding and spotting days usually decreases but bleeding may remain irregular.

Contraception Study

The amenorrhea rates observed in the LILETTA clinical study on contraception are shown in Table 2. The bleeding and spotting days, based on 28-day cycle equivalents, are shown in Table 3. In this study, 2.5% of participants discontinued LILETTA due to bleeding complaints.

Table 2: Amenorrhea Rates Last 90-Day Interval of Year
Year | 1 | 2 | 3 | 4 | 5 | 6 | 7 | 8
Amenorrhea Rate* | 19% | 27% | 37% | 37% | 40% | 40% | 39% | 39%

*Amenorrhea is defined as no bleeding and/or spotting.

Table 3: Bleeding and Spotting Days per 28-Day Cycle Equivalent
28-Day Cycle Equivalent N* | Cycle 1 N=1,691 |  | Cycle 4 N=1,593 |  | Cycle 7 N=1,519 |  | Cycle 13 N=1,395 |  | Cycle 26 N=1,109
Days on treatment | 1-28 |  | 85-112 |  | 169-196 |  | 337-364 |  | 674-728
 | Mean | SD | Mean | SD | Mean | SD | Mean | SD | Mean | SD
Number of bleeding days | 5.8 | 5.2 | 2.3 | 3.3 | 1.6 | 2.7 | 1.2 | 2.4 | 0.8 | 1.8
Number of spotting days | 9.0 | 5.9 | 4.3 | 4.2 | 3.2 | 3.6 | 2.7 | 3.4 | 1.9 | 2.8

*N includes all LILETTA participants in the clinical study on contraception.

Heavy Menstrual Bleeding Study

The amenorrhea rates observed in the LILETTA clinical study on heavy menstrual bleeding (HMB) are shown in Table 4. Amenorrhea developed in 19% of LILETTA study participants by Cycle 6.

Table 4: Amenorrhea Rates for 28-Day Treatment Cycles
28-Day Cycle N | Baseline N=87 | Cycle 1 N=87 | Cycle 2 N=88 | Cycle 3 N=88 | Cycle 4 N=82 | Cycle 5 N=82 | Cycle 6 N=79
Amenorrhea Rate* | 0% | 3% | 8% | 11% | 13% | 17% | 19%

*Amenorrhea is defined as no bleeding and/or spotting. Percentages within each cycle are based on the number of participants who completed the cycle.

The bleeding and spotting days, based on 28-day cycle equivalents, are shown in Table 5. In this study, 3.8% of LILETTA participants discontinued due to bleeding complaints.

Table 5: Bleeding and Spotting Days from Baseline to Treatment Cycle 3 and Cycle 6
28-Day Cycle N* | Baseline N=87 |  | Cycle 3 N=88 |  | Cycle 6 N=79
 | Mean | SD | Mean | SD | Mean | SD
Number of Bleeding Days | 4.9 | 1.5 | 3.7 | 3.8 | 2.2 | 3.5
Number of Spotting Days | 1.8 | 1.1 | 7.3 | 7.0 | 5.1 | 5.8

*N includes participants with at least one complete 28-day cycle of product-use. Calculations are based on complete 28-day cycles (at least 23 days in length).

Resumption of Menses After Discontinuation

In the LILETTA clinical study on contraception, 651 of 652 (99.8%) participants 16-35 years of age at enrollment that were evaluated resumed menses after LILETTA removal. This excludes twelve participants (9 became pregnant, 2 had a hysterectomy, and 1 had ovulatory dysfunction).

Other Bleeding Pattern Changes

If a significant change in bleeding develops during prolonged use, conduct diagnostic tests to assess possible endometrial pathology. Consider the possibility of pregnancy, including ectopic pregnancy, if menstruation does not occur within six weeks of the onset of a previous menstruation. After excluding pregnancy, repeat pregnancy tests are generally not necessary in amenorrheic patients unless indicated by other signs of pregnancy or pelvic pain.

5.9 Breast Cancer

Patients who currently have or have had breast cancer, or have a suspicion of breast cancer, should not use hormonal contraception, including LILETTA, because some breast cancers are hormone-sensitive [see Contraindications (4)].

Spontaneous reports of breast cancer have been received during postmarketing experience with LNG-releasing IUSs. Observational studies have not provided consistent evidence of an increased risk of breast cancer with use of an LNG-releasing IUS.

5.10 Clinical Considerations for Use and Removal

Obtain a complete medical and social history, including partner status, to determine conditions that might influence the selection of an IUS for contraception.

Exclude underlying endometrial pathology (e.g., polyps or cancer) prior to the insertion of LILETTA in patients with persistent or uncharacteristic bleeding because irregular bleeding/spotting is common during the first months of LILETTA use and may preclude adequate assessment after insertion. LILETTA is contraindicated in patients with uterine bleeding of unknown etiology.

Exclude underlying congenital or acquired uterine anomalies, including leiomyomas, that distort the uterine cavity and would be incompatible with correct IUS placement [see Contraindications (4)].

Ensure a previously inserted IUS has been removed prior to insertion of LILETTA [see Contraindications (4)].

Assess whether the patient is at increased risk of pelvic infection (e.g., unprotected sex, history of PID, or acquired immune deficiency syndrome [AIDS]). LILETTA does not protect against HIV/STI transmission [see Warnings and Precautions (5.4)].

Use LILETTA with caution after careful assessment if any of the following conditions exist, and consider removal of the IUS if any of them arise during use:

- Coagulopathy or use of anticoagulants
- Migraine, focal migraine with asymmetrical visual loss, or other symptoms indicating transient cerebral ischemia
- Exceptionally severe or frequent headache
- Marked increase of blood pressure
- Severe arterial disease such as stroke or myocardial infarction

Consider removing LILETTA if any of the following conditions arise during use [see Contraindications (4)]:

- Uterine or cervical malignancy
- Jaundice

If the threads are not visible or are significantly shortened, they may have broken or retracted into the cervical canal or uterus. Consider the possibility that the IUS may have been displaced, (e.g., expulsed or perforated the uterus) [see Warnings and Precautions (5.5, 5.6)]. Exclude pregnancy and verify the location of LILETTA by an appropriate diagnostic method (e.g., ultrasonography, X-ray, or gentle exploration of the cervical canal with a suitable instrument) [see Dosage and Administration (2.6)]. If LILETTA is displaced, remove it. A new LILETTA may be inserted at that time or during the next menses if it is certain that conception has not occurred. If LILETTA is in place with no evidence of perforation, no intervention is indicated.

5.11 Magnetic Resonance Imaging (MRI) Information

LILETTA is MR-Safe. LILETTA is compatible with MRI and should not interfere with imaging.

6 ADVERSE REACTIONS

The following serious or important adverse reactions are discussed elsewhere in the labeling:

Ectopic Pregnancy [see Warnings and Precautions (5.1)]

Intrauterine Pregnancy [see Warnings and Precautions (5.2)]

Group A Streptococcal Sepsis (GAS) [see Warnings and Precautions (5.3)]

Pelvic Inflammatory Disease or Endometritis [see Warnings and Precautions (5.4)]

Perforation [see Warnings and Precautions (5.5)]

Expulsion [see Warnings and Precautions (5.6)]

Ovarian Cysts [see Warnings and Precautions (5.7)]

Bleeding Pattern Alterations [see Warnings and Precautions (5.8)]

6.1 Clinical Study Experience

Because clinical studies are conducted under widely varying conditions, adverse reaction rates observed in the clinical studies of a drug cannot be directly compared to rates in the clinical studies of another drug and may not reflect the rates observed in practice.

The data described below reflect exposure of 1,751 generally healthy participants, 16 to 45 years of age, to LILETTA in a large, multi-center contraceptive study conducted in the US. Participants included 1,401 exposed for 1 year and 380 who completed 8 years of use; 58% were nulliparous (mean age 25.1 ± 4.3 years) and 42% were parous (mean age 30.3 ± 6.1 years). Most participants who received LILETTA were Caucasian (78.4%) or Black/African American (13.3%); 14.7% of participants were of Hispanic ethnicity. Mean BMI of LILETTA participants was 26.9 kg/m^2 (range 15.8 – 61.6 kg/m^2); 25.1% had a BMI ≥ 30 kg/m^2 of which 5.3% had a BMI ≥ 40 kg/m^2. The data cover more than 80,221 28-day cycles of LILETTA exposure. The frequencies of reported adverse drug reactions represent crude incidences.

The most common adverse reactions during the LILETTA clinical study on contraception (occurring in ≥ 5% of participants) are shown in Table 6. The most common adverse reactions during the first year of use were acne (11.4%), bacterial vaginitis (9.0%), and vulvovaginal mycotic infection (7.9%).

Table 6: Adverse Reactions in ≥ 5% of LILETTA Participants in the Phase 3 Clinical Study on Contraception
Adverse Reaction | % LILETTA Participants (N = 1,751)
Vulvovaginal mycotic infections | 20.2%
Vaginal bacterial infections | 19.2%
Acne | 15.5%
Nausea or vomiting | 10.5%
Headache | 10.1%
Breast tenderness or pain | 10.1%
Abdominal discomfort or pain | 10.0%
Dyspareunia | 9.6%
Anxiety | 9.6%
Depression | 9.1%
Pelvic discomfort or pain | 8.7%
Dysmenorrhea | 7.3%
Mood changes | 6.5%
Back pain | 6.5%
Weight increased | 6.1%
Vaginal discharge | 5.8%

In the clinical study, 20.1% of LILETTA participants discontinued prematurely due to an adverse reaction. The most common adverse reactions reported by participants as reason for discontinuation were expulsion (4.1%), bleeding complaints (2.5%), acne (1.4%), dysmenorrhea (1.0%), weight increased (1.0%), mood swings (0.8%), uterine spasm (0.7%), dyspareunia (0.6%) and pelvic pain (0.6%). Two participants discontinued the clinical study due to PID and one due to endometritis. The most common adverse reactions reported by participants as reason for discontinuation during the first year of use were expulsion (2.9%) and acne (0.7%).

In the clinical study, serious adverse reactions related to LILETTA were ectopic pregnancies, ovarian cysts, and IUS perforation requiring laparoscopic surgery.

In the LILETTA clinical study on heavy menstrual bleeding, which included 105 participants who were 18- to 50-years old, the adverse reaction profile was consistent with the adverse reaction profile for LILETTA participants in the contraception study as shown in Table 6. Approximately 11% of LILETTA study participants discontinued prematurely due to an adverse reaction. The most common adverse reactions leading to discontinuation were expulsions (4.8%) and bleeding pattern alterations (3.8%).

6.2 Postmarketing Experience

The following adverse reactions have been identified during post-approval use of LNG-releasing IUSs. Because these reactions are reported voluntarily from a population of uncertain size, it is not always possible to reliably estimate their frequency or establish a causal relationship to drug exposure.

- Arterial thrombotic and venous thromboembolic events, including cases of pulmonary emboli, deep vein thrombosis, and stroke
- Hypersensitivity (including rash, urticaria, and angioedema)
- Increased blood pressure
- Dizziness
- Device breakage

7 DRUG INTERACTIONS

No drug-drug interaction studies have been conducted with LILETTA.

8 USE IN SPECIFIC POPULATIONS

8.1 Pregnancy

Risk Summary

LILETTA is contraindicated for use in pregnant patients and LILETTA may cause adverse pregnancy outcomes. If a patient becomes pregnant with LILETTA in place, there is an increased risk of miscarriage, sepsis, premature labor, and premature delivery. Published studies report no harmful effects on fetal development associated with long-term use of contraceptive doses of oral progestins in a pregnant patient. There have been isolated cases of virilization of the external genitalia of the female fetus following local exposure to LNG during pregnancy with an LNG IUS in place. Animal reproduction studies have not been conducted with LILETTA.

The background risk in the U.S. general population of major birth defects is 2-4% and of miscarriage is 15-20% of clinically recognized pregnancies.

8.2 Lactation

Risk Summary

Published studies report the presence of LNG in human milk. Small amounts of progestins (approximately 0.1% of the total maternal doses) were detected in the breast milk of nursing mothers who used other LNG-releasing IUSs. Isolated cases of decreased milk production have been reported with another LNG-releasing IUS. There are no reports of adverse effects in breastfed infants with maternal use of progestin-only contraceptives. The infant’s developmental and health benefits of breastfeeding should be considered along with the mother’s clinical need for LILETTA, underlying maternal conditions, and any potential adverse effects from LILETTA on the infant.

The incidence of uterine perforation appears higher in lactating patients [see Warnings and Precautions (5.5)].

8.3 Females and Males of Reproductive Potential

Pregnancy Testing

Assess pregnancy status prior to inserting LILETTA, as recommended [see Dosage and Administration (2.2) and Use in Specific Populations (8.1)].

8.4 Pediatric Use

Safety and effectiveness of LILETTA have been established in females of reproductive potential. The safety and effectiveness are expected to be the same for postpubertal females under the age of 16 as for users 16 years and older. The LILETTA clinical study on contraception included 11 participants who were 16 to 17 years of age; no differences in safety or effectiveness were identified in these participants through 8 years of use of LILETTA. Use of this product is not indicated before menarche.

8.5 Geriatric Use

LILETTA is not indicated in patients after menopause and has not been studied in this population.

8.6 Hepatic Impairment

No studies were conducted to evaluate the effect of hepatic disease on the disposition of LNG released from LILETTA [see Contraindications (4)].

11 DESCRIPTION

11.1 LILETTA

LILETTA (levonorgestrel-releasing intrauterine system) contains 52 mg of levonorgestrel, a progestin, and is intended to provide an initial release rate of 20.4 mcg/day of levonorgestrel.

Levonorgestrel USP, (-)-13-ethyl-17-hydroxy-18,19-dinor-17α-pregn-4-en-20-yn-3-one, the active ingredient in LILETTA, is the levorotatory form of norgestrel, which consists of a racemic mixture of D-(–)-norgestrel (levonorgestrel) and L-(+)-norgestrel (dextronorgestrel). It has a molecular weight of 312.45, a molecular formula of C21H28O2, and the following structural formula:

LILETTA consists of a T-shaped polyethylene frame (T-frame) with a drug reservoir around the vertical stem (Figure 15). The T-frame has a loop at one end of the vertical stem and two horizontal arms at the other end. The drug reservoir consists of a cylinder, made of a mixture of 52 mg levonorgestrel and polydimethylsiloxane (PDMS) formed from silicone base, tetra-n-propyl silicate, and stannous octoate. The drug reservoir is covered by a translucent PDMS membrane. The low-density polyethylene of the T-frame is compounded with barium sulfate, which makes it radio-opaque. A blue polypropylene monofilament removal thread is attached to an eyelet at the end of the vertical stem of the T-frame. The polypropylene of the removal thread contains a copper-containing pigment as a colorant. The components of LILETTA, including its packaging, are not manufactured using natural rubber latex.

Figure 15: Diagram of LILETTA

11.2 Inserter

The inserter device provided with LILETTA is a single-use, disposable, sterile insertion system (tube, flange, handle; Figure 16), partially preloaded with the IUS product for intrauterine administration.

Once LILETTA has been inserted, the inserter is discarded.

Figure 16: Diagram of Inserter

12 CLINICAL PHARMACOLOGY

12.1 Mechanism of Action

The local mechanism by which continuously released LNG provides contraception has not been conclusively demonstrated. Studies of LNG-releasing IUSs suggest several mechanisms for pregnancy prevention: prevention of fertilization due to the thickening of the cervical mucus, which inhibits sperm passage through the cervix, and inhibition of sperm mobility and function (capacitation), and alteration of the endometrium.

12.2 Pharmacodynamics

LILETTA has mainly local progestogenic effects in the uterine cavity which change the endometrium and may lead to alterations in the menstrual bleeding pattern [see Warnings and Precautions (5.8)]. High local concentrations of LNG lead to morphological changes including stromal pseudo-decidualization, glandular atrophy, a leukocytic infiltration, and a decrease in glandular and stromal mitoses.

In clinical studies with other LNG-releasing IUSs with an LNG release rate similar to LILETTA, approximately 45-75% of menstrual cycles were ovulatory.

12.3 Pharmacokinetics

Absorption

Low doses of LNG are administered into the uterine cavity with the LILETTA intrauterine delivery system. The initial in vivo release rate is 20.4 mcg/day and decreases to 17.7 mcg/day at 1 year, 15.3 mcg/day at 2 years, 13.3 mcg/day at 3 years, 11.5 mcg/day at 4 years, 10.0 mcg/day at 5 years, 8.7 mcg/day at 6 years, 7.5 mcg/day at 7 years, and 6.5 mcg/day at 8 years.

In the clinical study on contraception, systemic plasma LNG concentrations were assessed in a subset of participants through Month 30 and in all participants in the study at Month 36 and after. Plasma LNG concentrations following insertion of LILETTA are shown in Table 7.

Table 7: Plasma LNG Concentrations (mean ± SD, pg/mL) Following LILETTA Insertion
7 Days (n=40) | 6 Months (n=36) | 12 Months (n=33) | 24 Months (n=30) | 36 Months (n=914) | 48 Months (n=793) | 60 Months (n=608) | 72 Months (n=243) | 84 Months (n=211) | 96 Months (n=142)
252±123 | 195±68 | 168±51 | 150±47 | 132±54 | 114±52 | 101±42 | 92±43 | 90±38 | 88±37

Distribution

The apparent volume of distribution of LNG at steady-state following oral administration is reported to be approximately 1.8 L/kg. It is about 98.9% protein-bound, principally to sex hormone binding globulin (SHBG) and, to a lesser extent, serum albumin.

Elimination

The elimination half-life of LNG after a single oral administration is approximately 13.9 ± 3.2 hours. Metabolic clearance rates may differ among individuals by several-fold, and this may account in part for wide individual variations in LNG concentrations seen in individuals using LNG–containing contraceptive products.

Metabolism

Following absorption, LNG is conjugated at the 17β-OH position to form sulfate conjugates and, to a lesser extent, glucuronide conjugates in serum. Significant amounts of conjugated and unconjugated 3α, 5β-tetrahydrolevonorgestrel are also present in serum, along with much smaller amounts of 3α, 5α-tetrahydrolevonorgestrel and 16β-hydroxylevonorgestrel. In vitro studies have demonstrated that oxidative metabolism of LNG is catalyzed by CYP enzymes, especially CYP3A4.

Excretion

About 45% of LNG and its metabolites are excreted in the urine and about 32% are excreted in feces, mostly as glucuronide conjugates.

Specific Populations

Racial or Ethnic Groups:

The effect of race on plasma LNG concentrations after LILETTA insertion was assessed in 731 (80%) White participants, 106 (12%) Black participants, 40 (4%) Asian participants, 8 (1%) American Indian/Alaska Native participants, and 21 (2%) multiple-race participants. Race does not appear to affect LNG concentrations following LILETTA insertion [see Clinical Studies (14)].

BMI/Body Weight:

The effect of BMI on LNG exposure was assessed in 687 non-obese (BMI < 30 kg/m^2) and 225 obese participants (BMI ≥ 30 kg/m^2). Plasma LNG concentrations were approximately 21-34% lower in obese participants than in non-obese participants based on data collected from Months 36 to 96. However, since LILETTA has a mainly local progestogenic effect in the uterine cavity, the clinical relevance of the reduced systemic exposure is unclear [see Clinical Studies (14)].

Drug Interaction Studies

Contraceptive effect of LILETTA is mediated via the direct release of LNG into the uterine cavity and is unlikely to be affected by drug interactions via enzyme induction or inhibition.

13 NONCLINICAL TOXICOLOGY

13.1 Carcinogenesis, Mutagenesis, Impairment of Fertility

[see Warnings and Precautions (5.9)]

14 CLINICAL STUDIES

14.1 Clinical Study on Contraception

The efficacy of LILETTA for contraception was studied in a multicenter, randomized, open-label clinical study conducted in the US that enrolled 1,910 generally healthy participants aged 16 to 45 years, 1,751 of whom received LILETTA. LILETTA was inserted in 1,011 (58%) nulliparous and 740 (42%) parous participants. Participants with a history of ectopic pregnancy, PID, or trophoblastic disease without a subsequent intrauterine pregnancy, who were less than 4 weeks post-pregnancy, had HIV, or were not in a mutually monogamous relationship at study entry were excluded. The demographic profile of enrolled participants who received LILETTA are as follows: White 78.4%, Black or African American 13.3%, Asian 3.9%, American Indian or Alaska Native 1.2%, Native Hawaiian or Other Pacific Islander 0.3%; 2.9% identified multiple races; 14.7% indicated Hispanic ethnicity. The clinical study had no limit on weight (minimum or maximum) or BMI (range was 15.8 – 61.6 kg/m^2). The mean BMI of LILETTA participants was 26.9 kg/m^2; 24% were overweight, 24% were obese (BMI ≥ 30 kg/m^2), and 5% were morbidly obese (BMI ≥ 40 kg/m^2).

The pregnancy rate calculated as the Pearl Index (PI) in participants 16 to 35 years of age, inclusive, was the primary efficacy endpoint used to assess contraceptive reliability. The PI was calculated based on 28-day equivalent exposure cycles; evaluable cycles excluded those in which back-up contraception was used unless a pregnancy occurred in that cycle. The Year 1 PI was based on two pregnancies and the cumulative 8-year pregnancy rate was calculated by the life table method, based on a total of eleven pregnancies that occurred after the onset of treatment and within 7 days after LILETTA removal or expulsion. Table 8 shows the annual PI for each of the eight years and the calculated cumulative life table pregnancy rates through years 1, 2, 3, 4, 5, 6, 7, and 8. For Year 7 and Year 8, participants who were more than 39 years of age at the beginning of the respective study year were excluded from the efficacy analysis.

Table 8: Contraceptive Efficacy: Pregnancy Rates
LILETTA Clinical Study | Number of 28-Day Cycles of Exposure By Year | Year-by-Year Pearl Index Pregnancy Rate (95% CI) | Cumulative 28-Day Cycles of Exposure | Cumulative Year Life Table Pregnancy Rate (95% CI)
Year 1 | 17,175 | 0.15 (0.02, 0.55) | 17,175 | 0.14 (0.04, 0.57)
Year 2 | 14,205 | 0.37 (0.10, 0.94) | 31,380 | 0.50 (0.22, 1.10)
Year 3 | 11,760 | 0.11 (0.00, 0.62) | 43,140 | 0.60 (0.29, 1.27)
Year 4 | 9,891 | 0.13 (0.00, 0.73) | 53,031 | 0.73 (0.36, 1.48)
Year 5 | 8,337 | 0.16 (0.00, 0.87) | 61,368 | 0.89 (0.45, 1.74)
Year 6 | 6,916 | 0.00 (0.00, 0.69) | 68,284 | 0.89 (0.45, 1.74)
Year 7* | 5,280 | 0.49 (0.06, 1.78) | 73,564 | 1.37 (0.71, 2.62)
Year 8* | 3,657 | 0.00 (0.00, 1.31) | 77,221 | 1.37 (0.71, 2.62)

*Excludes participants >39 years of age at the beginning of the respective year.

Conception rates after the removal of LILETTA were assessed and appeared consistent with conception rates in the general population having regular unprotected sexual intercourse for 12 months.

Of 244 participants who desired pregnancy after study discontinuation, 63.1% conceived within 6 months after removal of LILETTA and 83.2% conceived within 12 months after removal of LILETTA.

14.2 Clinical Study on Treatment of Heavy Menstrual Bleeding

The efficacy of LILETTA in the treatment of heavy menstrual bleeding was studied in a non-comparative, open-label clinical study conducted in the US. The study enrolled 105 generally healthy participants 18 to 50 years of age, with no contraindications to LILETTA, and with confirmed heavy menstrual bleeding (≥ 80 mL menstrual blood loss [MBL] per menses) determined using the alkaline hematin method. Participants with any structural (e.g., leiomyomas > 2 cm in greatest diameter or more than 3 leiomyomas > 1.5 cm in greatest diameter) or diagnosed pathophysiologic conditions that may cause heavy uterine bleeding were excluded.

The study population was 64.8% White, 23.8% African American, and 11.4% Other; 9.5% of enrolled participants were of Hispanic ethnicity. The median BMI was 29.7 kg/m^2 (with 23.8% overweight and 48.6% obese). The median baseline MBL was 143.2 mL.

The primary efficacy endpoint was the proportion of women with successful treatment, defined as (1) an end-of-study MBL volume < 80 mL and (2) ≥ 50% reduction in MBL from baseline to end-of-study.

Treatment outcomes with LILETTA are summarized in Figures 17 and 18. The proportion of participants meeting both criteria defining successful treatment was 80% at the end of the study, with a 95% confidence interval of 71-88% (Figure 17). The quantitative reduction in median MBL volume from baseline to mid-study and to end-of-study is shown in Figure 18. The median MBL percent reduction from baseline to mid-study was 91% and to end-of-study was 96%.

15 REFERENCES

(1) Centers for Disease Control and Prevention (CDC). CDC STI Treatment Guidelines [online] Available at: https://www.cdc.gov/std/treatment-guidelines/pid.htm

16 HOW SUPPLIED/STORAGE AND HANDLING

LILETTA (levonorgestrel-releasing intrauterine system), containing 52 mg levonorgestrel, is supplied partially preloaded within the inserter and packaged in a clear plastic tray with lid. LILETTA is available in a carton of one sterile unit. NDC # 0023-5858-01.

LILETTA is supplied sterile. LILETTA is sterilized with ethylene oxide. Do not re-sterilize. Do not use if the packaging is damaged, or if the packaging is opened. Insert before the end of the month shown on the packaging. Store at 20°C – 25°C (68°F – 77°F), with excursions permitted between 15°C – 30°C (59°F – 86°F) [See USP Controlled Room Temperature]. Store the sealed tray with peel-off lid in outer carton until use to protect from light.

17 PATIENT COUNSELING INFORMATION

Advise patients to read the FDA-approved patient labeling (Patient Information).

Advise patients that this product does not protect against HIV infection (AIDS) and other sexually transmitted infections (STIs).

Advise patients about the risks of ectopic pregnancy, including the loss of fertility. Advise them to recognize and report promptly to their healthcare professional any symptoms of ectopic pregnancy, including lower abdominal pain, especially in association with missed periods [see Warnings and Precautions (5.1)].

Advise patients about the following concerns and precautions if pregnancy occurs while using LILETTA:

- LILETTA will likely need to be removed because leaving it in place may increase the risk of spontaneous abortion and preterm labor; however, removal of LILETTA or probing of the uterus may also result in spontaneous abortion [see Warnings and Precautions (5.2)].
- Report promptly to their healthcare professional any symptoms that suggest complications of the pregnancy, including flu-like symptoms, fever, chills, cramping, pain, bleeding, and vaginal discharge or leakage of fluid [see Warnings and Precautions (5.2)].
- Septic abortion may occur. Advise them that if LILETTA cannot be removed or they choose not to have it removed, there may be an increased risk of miscarriage, sepsis, premature labor, and premature delivery [see Warnings and Precautions (5.2)].

Advise patients that severe infection or sepsis, including Group A streptococcal sepsis (GAS), can occur within the first few days after LILETTA is inserted. Advise them to contact a healthcare professional immediately if they develop severe pain or fever shortly after LILETTA is inserted [see Warnings and Precautions (5.3)].

Advise patients about the possibility of PID or endometritis and that these infections can cause tubal damage leading to ectopic pregnancy or infertility, or infrequently can necessitate hysterectomy, or cause death. Advise the patient to recognize and report to their healthcare professional any of the following signs and symptoms of possible infection [see Warnings and Precautions (5.4)]:

- lower abdominal or pelvic pain or tenderness
- fever
- chills
- unusual or malodorous vaginal discharge
- atypical or unexplained bleeding (prolonged or heavy bleeding)
- genital lesions or sores.
- dyspareunia

Advise patients that perforation may occur, most often during insertion, although the perforation may not be detected until sometime later. Perforation may also occur at any time during IUS use. Advise them that if perforation occurs, LILETTA will have to be located and removed. Surgery may be required. Advise them that delayed detection or removal of LILETTA in case of perforation may have the following results [see Warnings and Precautions (5.5)]:

- migration of IUS outside the uterus

- intestinal perforations

- adhesions

- intestinal obstruction

- peritonitis

- erosion of adjacent viscera

- abscesses

- loss of contraceptive protection

Review with patients the signs and symptoms of LILETTA expulsion. Advise patients on how they can check that the threads still protrude from their cervix, and not to pull on them. Advise them that there is no contraceptive protection if LILETTA is displaced or expelled [see Warnings and Precautions (5.6)].

Advise patients that excessive pain or vaginal bleeding during insertion, worsening pain or bleeding after insertion, or the inability to feel the threads may occur with perforation and expulsion [see Warnings and Precautions (5.5, 5.6)].

Advise patients regarding the risk of ovarian cysts and that cysts can cause clinical symptoms including pelvic pain, abdominal pain or dyspareunia and infrequently will need surgery [see Warnings and Precautions (5.7)].

Advise patients that irregular or prolonged bleeding and spotting, and/or cramps may occur during the first three to six months after insertion. If their symptoms continue or are severe, they should report them to their healthcare professional [see Warnings and Precautions (5.8)].

Advise patients to contact their healthcare professional if they experience any of the following symptoms or conditions:

- Stroke or heart attack
- Very severe or migraine headaches
- Unexplained fever
- Yellowing of the skin or whites of the eyes, as these may be signs of serious liver problems
- Pregnancy or suspected pregnancy
- Severe vaginal bleeding or bleeding that lasts a long time, or if they miss a menstrual period
- Pelvic pain or pain during sex
- Patient or partner becomes HIV positive
- Possible exposure to sexually transmitted infections (STIs)
- Unusual or malodorous vaginal discharge
- Genital sores
- Inability to feel LILETTA's threads

Inform patients that LILETTA is compatible with MRI and should not interfere with imaging [see Warnings and Precautions (5.11)].

LILETTA and its design are trademarks of Odyssea Pharma SPRL, an AbbVie company.

Medicines360 and its design are trademarks of Medicines360.

Manufactured by:
Odyssea Pharma, SPRL, Belgium
An affiliated company of AbbVie

Distributed by:
AbbVie Inc.
North Chicago, Illinois 60064

Marketed by:
AbbVie Inc. Medicines360
North Chicago, IL 60064 San Francisco, CA 94105

© 2023 AbbVie and Medicines360. All rights reserved.

V4.1USPI5858

PATIENT INFORMATION
LILETTA (lye-LET-uh)
(levonorgestrel-releasing intrauterine system)

Read this Patient Information carefully before you decide if LILETTA is right for you. This information does not take the place of talking with your gynecologist or other healthcare professional. If you have any questions about LILETTA, ask your healthcare professional. You should also learn about other birth control methods to choose the one that is best for you.

LILETTA does not protect against HIV infection (AIDS) and other sexually transmitted infections (STIs).

What is LILETTA?

- LILETTA is a hormone-releasing system placed in your uterus by your healthcare professional to prevent pregnancy for up to 8 years.
- LILETTA can also help with heavy periods, also known as heavy menstrual bleeding (HMB), for up to 5 years.
- LILETTA can be removed by your healthcare professional at any time.
- LILETTA can be used whether or not you have given birth to a child.

LILETTA is a small, flexible plastic T-shaped system that slowly releases a progestin hormone called levonorgestrel (LNG) that is often used in birth control pills. Because LILETTA releases LNG into your uterus, only small amounts of the hormone enter your blood. LILETTA does not contain estrogen.
Two thin threads are attached to the stem (lower end) of LILETTA. The threads are the only part of LILETTA you can feel when LILETTA is in your uterus; however, unlike a tampon string, the threads do not extend outside your body.

LILETTA is small

and flexible

What if I need birth control for more than 8 years?
LILETTA must be removed after 8 years. Your healthcare professional can place a new LILETTA during the same office visit if you choose to continue using LILETTA.

What if I need treatment for heavy menstrual flow for more than 5 years?
For continued treatment of heavy menstrual flow after 5 years, your healthcare professional can remove LILETTA and place a new LILETTA during the same office visit.

What if I want to stop using LILETTA?
LILETTA is intended for use as birth control for up to 8 years, but you can stop using LILETTA at any time by asking your healthcare professional to remove it. You could become pregnant as soon as LILETTA is removed, so you should use another method of birth control if you do not want to become pregnant. Talk to your healthcare professional about the best birth control methods for you, because your new method may need to be started 7 days before LILETTA is removed to prevent pregnancy.

What if I change my mind about birth control and want to become pregnant in less than 8 years?
Your healthcare professional can remove LILETTA at any time. You could become pregnant as soon as LILETTA is removed. About 5 out of 6 patients who want to become pregnant will become pregnant sometime in the first year after LILETTA is removed.

How does LILETTA work for birth control?
LILETTA may work in several ways including thickening cervical mucus, inhibiting sperm movement, reducing sperm survival, and thinning the lining of your uterus. It is not known exactly how these actions work together to prevent pregnancy.

How does LILETTA work for heavy menstrual bleeding?
The hormone in LILETTA, levonorgestrel, acts by controlling the monthly development of the womb (uterus) lining, making it thinner, so that there is less bleeding every month.

How well does LILETTA work for birth control?
The following chart shows the chance of getting pregnant for patients who use different methods of birth control. Each box on the chart contains a list of birth control methods that are similar in effectiveness. The most effective methods are at the top of the chart. The box on the bottom of the chart shows the chance of getting pregnant for patients who do not use birth control and are trying to get pregnant.
LILETTA, an intrauterine system (IUS), is also known as an intrauterine device (IUD), which is shown in the box at the top of the chart.

How well does LILETTA work for treating heavy menstrual bleeding?
In the clinical trial performed in patients with heavy menstrual bleeding and treated with LILETTA, the majority of (or 8 out of 10) patients were treated successfully. That is, their menstrual cycle blood loss was reduced to less than 80 mL and reduced by more than half by the end of treatment at six months.

Who might use LILETTA?
You might choose LILETTA if you are willing to use a birth control method that is placed in the uterus, and want birth control with the following features:

- long-term birth control that provides a low chance of getting pregnant (less than 1 in 100)
- works continuously for up to 8 years
- is reversible
- does not need to be taken daily
- does not contain estrogen
- treats heavy menstrual bleeding

Do not use LILETTA if you have any of the following conditions:

- you are or might be pregnant; LILETTA cannot be used as an emergency contraceptive
- a serious pelvic infection called pelvic inflammatory disease (PID)
- an untreated lower genital infection now
- a serious pelvic infection after an abortion or pregnancy within the last 3 months
- a condition or behavior that can allow you to get infections more easily, such as those listed below:
  ○ problems with your immune system
  ○ having multiple sexual partners or your partner has multiple sexual partners
  ○ history of PID
- cancer of the uterus or cervix, known or suspected
- bleeding from the vagina that has not been explained
- short-term (acute) liver disease or a liver tumor
- breast cancer or any other cancer that is sensitive to progestin (a female hormone), now or in the past
- an intrauterine contraceptive system in your uterus already
- a condition of the uterus that changes the shape of the uterine cavity, such as large fibroid tumors
- an allergy to levonorgestrel, silicone, polyethylene, or barium sulfate

Before having LILETTA placed, tell your healthcare professional if you have or had any medical conditions, including those listed below:

- any of the conditions listed above
- you recently had a baby, or you are breastfeeding
- heart attack
- stroke
- heart disease you were born with, or problems with your heart valves
- blood clotting problems, or condition for which you take medicine to reduce clotting
- high blood pressure
- severe migraine headaches
- severe or frequent headaches
- AIDS, HIV, or any other sexually transmitted infection

Tell your healthcare professional about all the medicines you take, including prescription and over-the-counter medicines, vitamins, and herbal supplements.

How is LILETTA placed?
LILETTA is placed by your healthcare professional during an in-office visit.
First, your healthcare professional will examine your pelvis to find the exact position of your uterus. Your healthcare professional will then clean your vagina and cervix with an antiseptic solution and slide a plastic tube containing LILETTA through the cervix into your uterus. Your healthcare professional will then remove the plastic tube and leave LILETTA in your uterus. Your healthcare professional will trim the threads to the right length.
You may experience pain, bleeding, or dizziness during and after placement. If your symptoms do not pass within 30 minutes after placement, LILETTA may not have been placed correctly. Your healthcare professional will examine you to see if LILETTA needs to be removed or replaced.

Should I check that LILETTA is in place?
Yes, you should check that LILETTA is in proper position by feeling the threads. It is a good habit to do this 1 time a month. Your healthcare professional should teach you how to check that LILETTA is in place. First, wash your hands with soap and water. You can check by reaching up to the top of your vagina with clean fingers to feel the threads. Do not pull on the threads.
If you feel more than just the threads or if you cannot feel the threads, LILETTA may not be in the right position and may not prevent pregnancy. Use non-hormonal back-up birth control (such as condoms) and ask your healthcare professional to check that LILETTA is still in the right place.

How soon after placement of LILETTA should I return to my healthcare professional?
Call your healthcare professional if you have any questions or concerns (see “When should I call my healthcare professional?”). Generally, patients have a follow-up visit 4 to 6 weeks after LILETTA is placed to make sure that LILETTA is in the right position, and routine visits thereafter. Follow-up plans may vary according to patient needs.

Can I use tampons or menstrual cups with LILETTA?
Yes, tampons or menstrual cups may be used with LILETTA. Change tampons or menstrual cups with care to avoid pulling the threads of LILETTA. If you think you may have pulled LILETTA out of place, avoid intercourse or use a non-hormonal back-up birth control (such as condoms), and contact your healthcare professional.

What if I become pregnant while using LILETTA?
Call your healthcare professional right away if you think you are pregnant. If possible, also do a urine pregnancy test. If you get pregnant while using LILETTA, you may have an ectopic pregnancy. This means that the pregnancy is not in the uterus. Unusual vaginal bleeding or abdominal pain, especially with missed periods, may be a sign of ectopic pregnancy.
Ectopic pregnancy is a medical emergency that often requires surgery. Ectopic pregnancy can cause internal bleeding, infertility, and even death.
There are also risks if you get pregnant while using LILETTA and the pregnancy is in the uterus. Severe infection, miscarriage, premature labor, premature delivery, and even death can occur with pregnancies that continue with an intrauterine system (IUS). Because of this, your healthcare professional may try to remove LILETTA, even though removing it may cause a miscarriage. If LILETTA cannot be removed, talk with your healthcare professional about the benefits and risks of continuing the pregnancy.
If you continue your pregnancy, see your healthcare professional regularly. Call your healthcare professional right away if you get flu-like symptoms, fever, chills, cramping, pain, bleeding, vaginal discharge, or fluid leaking from your vagina. These may be signs of infection.
It is not known if LILETTA can cause long-term effects on the fetus if it stays in place during a pregnancy.

How will LILETTA change my periods?
For the first 3 to 6 months, your period may become irregular and the number of bleeding days may increase. You may also have frequent spotting or light bleeding and cramping. Some patients have heavy bleeding during this time. After you have used LILETTA for a while, the number of bleeding and spotting days is likely to lessen. For some patients, menstrual periods will stop altogether. When LILETTA is removed, your menstrual periods will likely return to their former pattern.

Is it safe to breastfeed while using LILETTA?
You may use LILETTA when you are breastfeeding. LILETTA is not likely to affect the quality or amount of your breast milk or the health of your nursing baby. However, isolated cases of decreased milk production have been reported among patients using progestin-only birth control pills. The risk of LILETTA becoming attached to (embedded) or going through the wall of the uterus is increased when LILETTA is inserted while you are breastfeeding.

Will LILETTA interfere with sexual intercourse?
You and your partner should not feel LILETTA during intercourse. LILETTA is placed in the uterus, not in the vagina. In some cases, your partner may feel the threads. If this occurs, or if you or your partner experience pain during sex, talk with your healthcare professional.

Can I have a magnetic resonance imaging (MRI) procedure with LILETTA in place?
Yes, LILETTA should not interfere with imaging. Tell your healthcare professional you have an intrauterine contraceptive in place.

What are the possible side effects of LILETTA?
LILETTA can cause serious side effects, including those listed below:

- ectopic pregnancy. If you get pregnant while using LILETTA, you might have an ectopic pregnancy. This means that the pregnancy is not in the uterus. Unusual vaginal bleeding or abdominal pain, especially with missed periods, may be a sign of ectopic pregnancy. Ectopic pregnancy is a medical emergency that often requires surgery. Ectopic pregnancy can cause internal bleeding, infertility, and even death.
- intrauterine pregnancy risks. There are also risks if you get pregnant while using LILETTA and the pregnancy is in the uterus. Severe infection, miscarriage, premature labor, premature delivery, and even death can occur with pregnancies that continue with an intrauterine system (IUS). Because of this, your healthcare professional may try to remove LILETTA, even though removing it may cause a miscarriage. If LILETTA cannot be removed, talk with your healthcare professional about the benefits and risks of continuing the pregnancy. If, after seeing your healthcare professional, you choose to continue your pregnancy, see your healthcare professional regularly. Call your healthcare professional right away if you get flu-like symptoms, fever, chills, cramping, pain, bleeding, vaginal discharge, or fluid leaking from your vagina. These may be signs of infection. It is not known if LILETTA can cause long-term effects on the fetus if it stays in place during a pregnancy.
- life-threatening infection. Life-threatening infection can occur within the first few days after LILETTA is placed. Call your healthcare professional immediately if you develop severe pain or fever shortly after LILETTA is placed.
- pelvic inflammatory disease (PID) or endometritis. Some IUS users get a serious pelvic infection called pelvic inflammatory disease (PID) or endometritis. PID and endometritis may be sexually transmitted. You have a higher chance of getting PID or endometritis if you or your partner have sex with other partners. PID or endometritis can cause serious problems such as infertility, ectopic pregnancy, or pelvic pain that does not go away. PID is usually treated with antibiotics. More serious cases of PID or endometritis may require surgery. Removal of the uterus (hysterectomy) is sometimes needed. In rare cases, infections that start as PID or endometritis can even cause death.
  Tell your healthcare professional right away if you have any of these signs of PID or endometritis: long-lasting or heavy bleeding, unusual or foul-smelling vaginal discharge, low abdominal or pelvic pain, painful sex, genital lesions or sores, chills, or fever.
- perforation. LILETTA may partially go into the wall of the uterus (become embedded) or go completely through the wall of the uterus (perforate). If this occurs, LILETTA may no longer prevent pregnancy. If perforation occurs, LILETTA may move outside the uterus and can cause internal scarring, infection, or damage to other organs. You may need surgery to have LILETTA removed if it is embedded or perforation occurs. The risk of perforation is increased in breastfeeding patients.
- expulsion. LILETTA may come out of your uterus (expulsion). Expulsion occurs in about 4 out of 100 patients, most often in the first year of use. You may become pregnant if LILETTA comes out. If you think that LILETTA has come out, use another birth control method (such as condoms) or do not have sex (vaginal intercourse) until you are seen by a healthcare professional.
- cysts on the ovary. Some patients using LILETTA develop a cyst on the ovary. These cysts usually disappear on their own in 2 to 3 months. However, a cyst can cause pain and sometimes will need surgery.
- changes in bleeding. You may have bleeding and spotting between menstrual periods, especially during the first 3 to 6 months. Sometimes the bleeding is heavier than usual at first. Over time the bleeding often becomes lighter than usual and may be irregular. Call your healthcare professional if the bleeding remains heavier than usual or increases after it has been light for a while.

LILETTA’s most common side effects are listed below:

• acne

• vaginal discharge

• headache

• vaginal bacterial infection

• breast pain

• yeast infection of your vulva and vagina (vulvovaginal)

• abdominal pain

• nausea or vomiting

• pelvic pain

• weight increase

• menstrual-like cramping

• mood changes

• pain during sex

• anxiety

• back pain

• depression

- Pain, bleeding, or dizziness during and after placement. If these symptoms do not stop within 30 minutes after placement, LILETTA may not have been placed correctly, or they may be symptoms of perforation or expulsion. Your healthcare professional will examine you to see if LILETTA needs to be removed or replaced.
- Missed menstrual periods. About 2 out of 10 patients stop having periods after 1 year of LILETTA use. If you have any concerns that you may be pregnant while using LILETTA, do a urine pregnancy test and call your healthcare professional. When LILETTA is removed, your menstrual periods will usually return to your previous pattern.

These are not all the possible side effects of LILETTA. For more information, ask your healthcare professional or pharmacist.
Call your doctor for medical advice about side effects. You may report side effects to FDA at 1-800-FDA-1088.
You may also report side effects to AbbVie at 1-800-678-1605.

After LILETTA has been placed, when should I call my healthcare professional?
Call your healthcare professional if you have any concerns about LILETTA. Be sure to call if you have any of the conditions listed below:

- are pregnant or think you are pregnant
- pelvic pain or pain during sex
- unusual or foul-smelling vaginal discharge or genital sores
- unexplained fever, chills, or flu-like symptoms
- might be exposed to sexually transmitted infections (STIs)
- concern that LILETTA may have come out or expelled
- cannot feel LILETTA's threads
- very severe or migraine headaches
- yellowing of the skin or whites of the eyes (these may be signs of liver problems)
- stroke or heart attack
- you or your partner become HIV positive
- severe vaginal bleeding, bleeding that lasts a long time, or you miss your period

General information about the safe and effective use of LILETTA.
Medicines are sometimes prescribed for purposes other than those listed in a Patient Information leaflet.
You can ask your pharmacist or healthcare professional for information about LILETTA that is written for health professionals.
For more information, go to www.LILETTA.com or call 1-855-LILETTA (1-855-545-3882).

LILETTA and its design are trademarks of Odyssea Pharma SPRL, an AbbVie company.
Medicines360 and its design are trademarks of Medicines360.
Manufactured by:
Odyssea Pharma, SPRL, Belgium
An affiliated company of AbbVie
Distributed by:
AbbVie Inc.
North Chicago, Illinois 60064
Marketed by:
AbbVie Inc. Medicines360
North Chicago, IL 60064 San Francisco, CA 94105
© 2023 AbbVie and Medicines360. All rights reserved.

This Patient Information has been approved by the U.S. Food and Drug Administration 06/2023

V 4.0 PPI5858

PRINCIPAL DISPLAY PANEL

NDC 0023-5858-01
Rx Only
LILETTA®
(levonorgestrel-releasing intrauterine system) 52 mg
Single-Handed Insertion Device
1 Sterile Unit
Intrauterine use
abbvie/Medicine 360